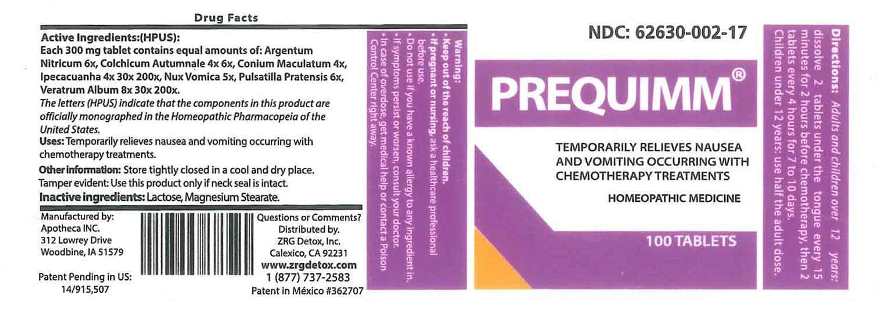 DRUG LABEL: Prequimm
NDC: 62630-002 | Form: TABLET
Manufacturer: ZRG Detox, Inc.
Category: homeopathic | Type: HUMAN OTC DRUG LABEL
Date: 20210824

ACTIVE INGREDIENTS: SILVER NITRATE 6 [hp_X]/1 1; COLCHICUM AUTUMNALE BULB 4 [hp_X]/1 1; CONIUM MACULATUM FLOWERING TOP 4 [hp_X]/1 1; IPECAC 4 [hp_X]/1 1; STRYCHNOS NUX-VOMICA SEED 5 [hp_X]/1 1; PULSATILLA PRATENSIS WHOLE 6 [hp_X]/1 1; VERATRUM ALBUM ROOT 8 [hp_X]/1 1
INACTIVE INGREDIENTS: LACTOSE MONOHYDRATE; MAGNESIUM PALMITOSTEARATE

DRUG FACTS:

ACTIVE INGREDIENTS:

Each 300mg tablet contains equal amounts of: Argentum Nitricum 6X, Colchicum Autumnale 4X, 6X, Conium Maculatum 4X, Ipecacuanha 4X, 30X, 200X, Nux Vomica 5X, Pulsatilla (Pratensis)6X, Veratrum Album 8X, 30X, 200X.

PURPOSE:

Temporarily relieves nausea and vomiting occurring with chemotherapy treatments.

WARNINGS:

Keep out of reach of children.

If pregnant or nursing, ask a healthcare professional before use.

Do not use if you have a known allergy to any ingredient in.

If symptoms persist or worsen, consult your doctor.

In case of overdose, get medical help or contact a Poison Control Center right away.

KEEP OUT OF REACH OF CHILDREN:

DIRECTIONS:

Adults and children over 12 years:

dissolve 2 tablets under the tongue every 15 minutes for 2 hours before chemotherapy,

then 2 tablets every 4 hours for 7 to 10 days.

Children under 12 years: use half the adult dose.

OTHER INFORMATION:

Store tightly closed in a cool and dry place.

Tamper evident: Use this product only if neck seal is intact.

INDICATIONS:

Temporarily relieves nausea and vomiting occurring with chemotherapy treatments.

INACTIVE INGREDIENTS:

Lactose, Magnesium Stearate.

QUESTIONS:

Distributed by.

ZRG Detox, Inc.

Calexico, CA 92231

www.zrgdetox.com

1 (877)737-2583

PACKAGE LABEL DISPLAY:

NDC: 62630-002-17

PREQUIMM

TEMPORARILY RELIEVES NAUSEA

AND VOMITING OCCURRING WITH

CHEMOTHERAPY TREATMENTS

HOMEOPATHIC MEDICINE

100TABLETS